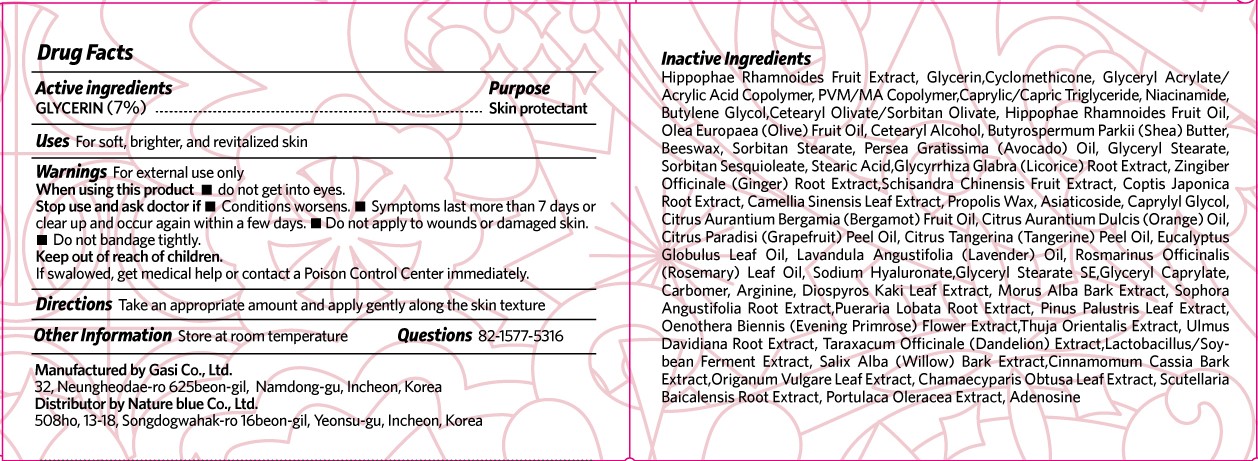 DRUG LABEL: SKINBUTAK GO YOUNG MAGICCREAM
NDC: 81851-202 | Form: CREAM
Manufacturer: NatureBlue Co.,Ltd
Category: otc | Type: HUMAN OTC DRUG LABEL
Date: 20210428

ACTIVE INGREDIENTS: GLYCERIN 7 mg/100 mL
INACTIVE INGREDIENTS: CYCLOMETHICONE; BUTYLENE GLYCOL; CETOSTEARYL ALCOHOL; SHEA BUTTER; YELLOW WAX; GLYCERYL MONOSTEARATE; GINGER; COPTIS JAPONICA ROOT; PROPOLIS WAX; ASIATICOSIDE; EUCALYPTUS OIL; HYALURONATE SODIUM; GLYCERYL STEARATE SE; ARGININE; DIOSPYROS KAKI LEAF; PLATYCLADUS ORIENTALIS SEED; SALIX ALBA BARK; CHAMAECYPARIS OBTUSA LEAF; ADENOSINE; HIPPOPHAE RHAMNOIDES FRUIT OIL; PURSLANE; MEDIUM-CHAIN TRIGLYCERIDES; OLIVE OIL; SORBITAN MONOSTEARATE; STEARIC ACID; GREEN TEA LEAF; BERGAMOT OIL; MANDARIN OIL; LAVENDER OIL; GLYCERYL CAPRYLATE; GLYCYRRHIZA GLABRA; CAPRYLYL GLYCOL; ORANGE OIL, COLD PRESSED; MORUS ALBA BARK; SOPHORA FLAVESCENS ROOT; PINUS PALUSTRIS LEAF; OENOTHERA BIENNIS FLOWER; TARAXACUM OFFICINALE; OREGANO; SCUTELLARIA BAICALENSIS ROOT; HIPPOPHAE RHAMNOIDES FRUIT; NIACINAMIDE; SORBITAN SESQUIOLEATE; SCHISANDRA CHINENSIS FRUIT; ULMUS DAVIDIANA ROOT; PUERARIA MONTANA VAR. LOBATA ROOT; CETEARYL OLIVATE; AVOCADO OIL; GRAPEFRUIT OIL; ROSEMARY OIL; CARBOMER HOMOPOLYMER, UNSPECIFIED TYPE; CHINESE CINNAMON

81851-202 SKINBUTAK GO YOUNG MAGIC CREAM

Active ingredients

GLYCERIN (7%)

Purpose

Skin protectant

Uses

For soft, brighter, and revitalized skin

Warnings

For external use only.

If swalowed, get medical help or contact a Poison Control Center immediately.

When using this product

- do not get into eyes.

Stop use and ask doctor if

- Conditions worsens.
- Symptoms last more than 7 days or clear up and occur again within a few days.
- Do not apply to wounds or damaged skin.
- Do not bandage tightly.

Keep out of reach of children.

Directions

Take an appropriate amount and apply gently along the skin texture

Inactive Ingredients

Hippophae Rhamnoides Fruit Extract, Glycerin,Cyclomethicone, Glyceryl Acrylate/ Acrylic Acid Copolymer, PVM/MA Copolymer,Caprylic/Capric Triglyceride, Niacinamide, Butylene Glycol,Cetearyl Olivate/Sorbitan Olivate, Hippophae Rhamnoides Fruit Oil, Olea Europaea (Olive) Fruit Oil, Cetearyl Alcohol, Butyrospermum Parkii (Shea) Butter, Beeswax, Sorbitan Stearate, Persea Gratissima (Avocado) Oil, Glyceryl Stearate, Sorbitan Sesquioleate, Stearic Acid,Glycyrrhiza Glabra (Licorice) Root Extract, Zingiber Officinale (Ginger) Root Extract,Schisandra Chinensis Fruit Extract, Coptis Japonica Root Extract, Camellia Sinensis Leaf Extract, Propolis Wax, Asiaticoside, Caprylyl Glycol, Citrus Aurantium Bergamia (Bergamot) Fruit Oil, Citrus Aurantium Dulcis (Orange) Oil, Citrus Paradisi (Grapefruit) Peel Oil, Citrus Tangerina (Tangerine) Peel Oil, Eucalyptus Globulus Leaf Oil, Lavandula Angustifolia (Lavender) Oil, Rosmarinus Officinalis (Rosemary) Leaf Oil, Sodium Hyaluronate,Glyceryl Stearate SE,Glyceryl Caprylate, Carbomer, Arginine, Diospyros Kaki Leaf Extract, Morus Alba Bark Extract, Sophora Angustifolia Root Extract,Pueraria Lobata Root Extract, Pinus Palustris Leaf Extract, Oenothera Biennis (Evening Primrose) Flower Extract,Thuja Orientalis Extract, Ulmus Davidiana Root Extract, Taraxacum Officinale (Dandelion) Extract,Lactobacillus/Soybean Ferment Extract, Salix Alba (Willow) Bark Extract,Cinnamomum Cassia Bark Extract,Origanum Vulgare Leaf Extract, Chamaecyparis Obtusa Leaf Extract, Scutellaria Baicalensis Root Extract, Portulaca Oleracea Extract, Adenosine

Other Information

Store at room temperature